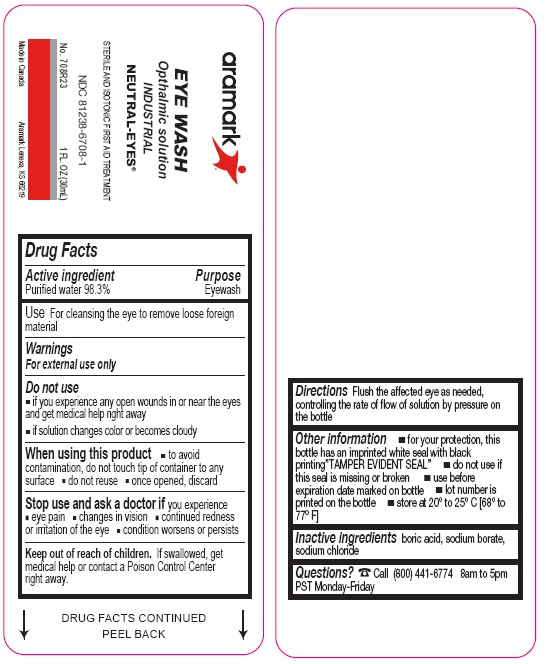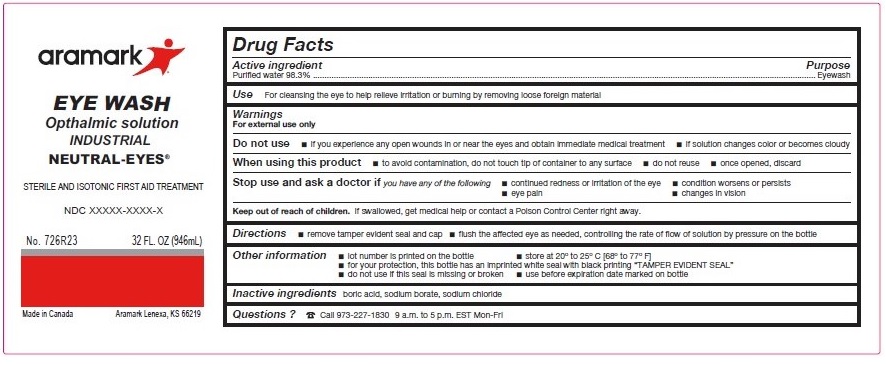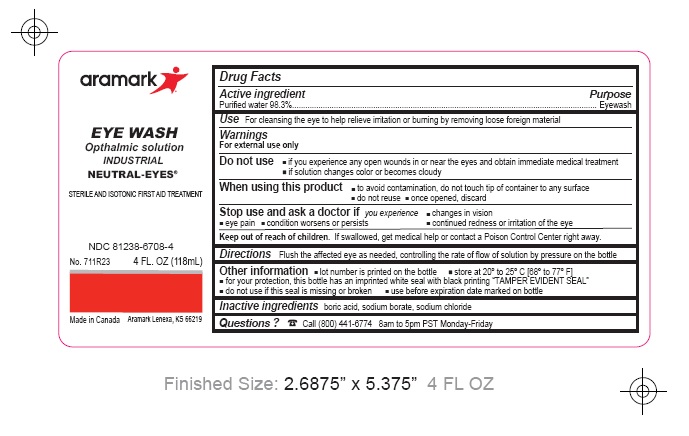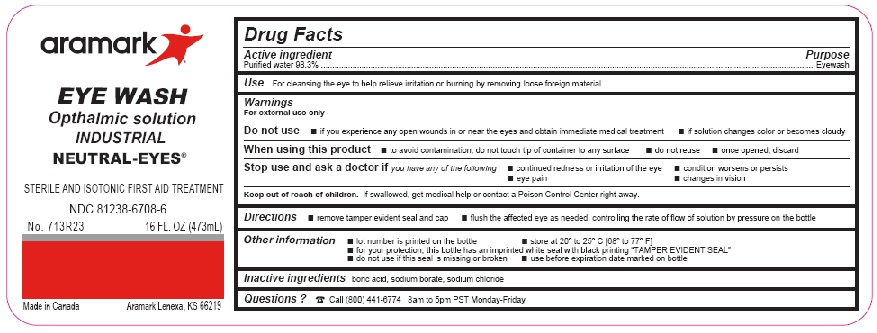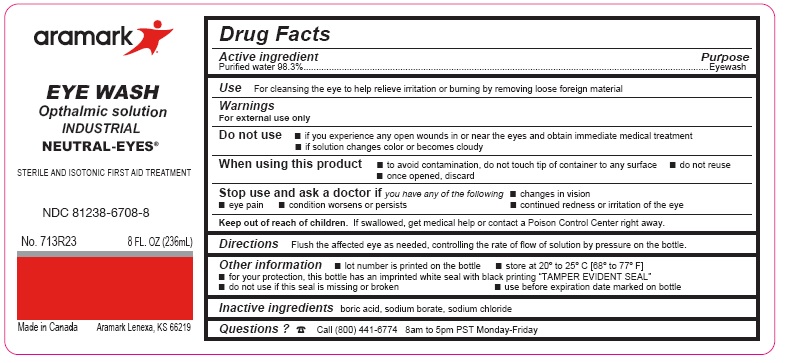 DRUG LABEL: Neutral-Eyes
NDC: 81238-6708 | Form: SOLUTION
Manufacturer: Western First Aid Safety
Category: otc | Type: HUMAN OTC DRUG LABEL
Date: 20210518

ACTIVE INGREDIENTS: WATER 98.3 g/100 mL
INACTIVE INGREDIENTS: BORIC ACID; SODIUM BORATE; SODIUM CHLORIDE

aramark Neutral-Eyes

Active Ingredients

Purified Water 98.3%

Purpose

Eyewash

INDICATIONS AND USAGE

Use For cleansing the eye to remove loose foreign
material

Warnings

For external use only

Do not use■ if you experience any open wounds in or near the eyes
and get medical help right away
■ if solution changes color or becomes cloudy

When using this product ■ to avoid
contamination, do not touch tip of container to any
surface ■ do not reuse ■ once opened, discard

Stop use and ask a doctor if you experience
■ eye pain ■ changes in vision ■ continued redness
or irritation of the eye ■ condition worsens or persists

Keep out of reach of children. If swallowed, get
medical help or contact a Poison Control Center
right away.

DOSAGE AND ADMINISTRATION

Directions Flush the affected eye as needed,
controlling the rate of flow of solution by pressure on
the bottle

Other information ■ for your protection, this
bottle has an imprinted white seal with black
printing”TAMPER EVIDENT SEAL” ■ do not use if
this seal is missing or broken ■ use before
expiration date marked on bottle ■ lot number is
printed on the bottle ■ store at 20º to 25º C [68º to
77º F]

Inactive ingredients boric acid, sodium borate,
sodium chloride

Questions? Call (800) 441-6774 8am to 5pm
PST Monday-Friday

Product Labeling

aramark

EYE WASH

Ophthalmic solution

INDUSTRIAL

NEUTRAL-EYES®

STERILE AND ISOTONIC FIRST AID TREATMENT

Mo. 708R23 1 FL. OZ (30mL)

Made in Canada Aramark Lenexa, KS 66219

1 FL OZ

4 FL OZ

8 FL OZ

16 FL OZ

32 FL OZ

res